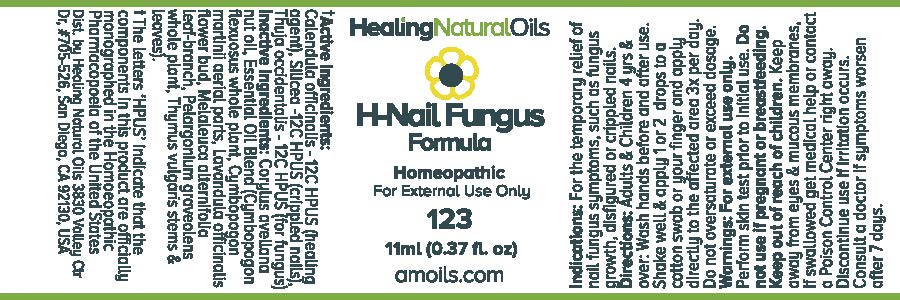 DRUG LABEL: H-Nail Fungus Formula
                
NDC: 61077-123 | Form: OIL
Manufacturer: Healing Natural Oils LLC
Category: homeopathic | Type: HUMAN OTC DRUG LABEL
Date: 20171227

ACTIVE INGREDIENTS: CALENDULA OFFICINALIS FLOWERING TOP 12 [hp_C]/11 mL; SILICON DIOXIDE 12 [hp_C]/11 mL; THUJA OCCIDENTALIS LEAFY TWIG 12 [hp_C]/11 mL
INACTIVE INGREDIENTS: EUROPEAN HAZELNUT OIL; CYMBOPOGON FLEXUOSUS WHOLE; CYMBOPOGON MARTINI TOP; LAVANDULA ANGUSTIFOLIA FLOWERING TOP; MELALEUCA ALTERNIFOLIA LEAF; PELARGONIUM GRAVEOLENS WHOLE; THYME

Active Ingredients:

Calendula officinalis - 12C HPUS
Silicea -12C HPUS
Thuja occidentalis - 12C HPUS

Purpose

Calendula officinalis - 12C HPUS (healing agent)
Silicea -12C HPUS (crippled nails)
Thuja occidentalis - 12C HPUS (for fungus)
The letters ‘HPUS’ indicate that the components in this product are officially
monographed in the Homoeopathic Pharmacopoeia of the United States

Inactive Ingredients:

Corylus avellana nut oil, Essential Oil Blend (Cymbopogon flexuosus whole plant, Cymbopogon martinii
aerial parts, Lavandula officinalis flower bud, Melaleuca alternifolia leaf-branch, Pelargonium graveolens whole plant,
Thymus vulgaris stems and leaves)

Indications:

For the temporary relief of nail fungus symptoms, such as fungus growth, disfigured or crippled nails.

Directions:

Adults and Children 4 yrs and over: Wash hands before and after use.
Shake well and apply 1 or 2 drops to a cotton swab or your finger and apply directly to the affected area 3x per day.
Do not oversaturate or exceed dosage.

Warnings:

For external use only.
Perform skin test prior to initial use.

Do not use if pregnant or breastfeeding.

Keep out of reach of children.

OTHER SAFETY INFORMATION

Keep away from eyes and mucous membranes. If swallowed get medical help or contact a Poison Control
Center right away.

Discontinue use if irritation occurs.

ASK DOCTOR

Consult a doctor if symptoms worsen after 7 days.

DESCRIPTION

Dist. by Healing Natural Oils 3830 Valley Ctr Dr, #705-526, San Diego, CA 92130, USA

PACKAGE LABEL

Healing Natural Oils

H-Nail Fungus
Formula

Homeopathic

For External Use Only

123

11ml (0.37 fl. oz)
amoils.com